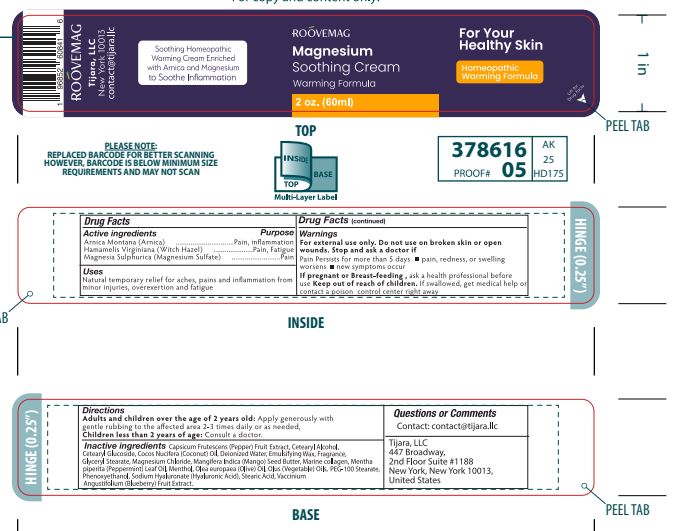 DRUG LABEL: ROOVEMAG Magnesium Soothing Warming Cream
NDC: 76348-403 | Form: CREAM
Manufacturer: RENU LABORATORIES, INC.
Category: homeopathic | Type: HUMAN OTC DRUG LABEL
Date: 20230208

ACTIVE INGREDIENTS: HAMAMELIS VIRGINIANA ROOT BARK/STEM BARK 0.6 g/60 g; ARNICA MONTANA 0.6 g/60 g; MAGNESIUM SULFATE HEPTAHYDRATE 0.12 g/60 g
INACTIVE INGREDIENTS: HYALURONIC ACID; MARINE COLLAGEN, SOLUBLE; GRAPEFRUIT; WHITE WAX; COCONUT OIL; OLIVE OIL; MANGIFERA INDICA SEED BUTTER; LAURETH-7; CAPSICUM; SHEA BUTTER; PEPPERMINT OIL; MAGNESIUM CHLORIDE; CORN OIL; WATER; CETOSTEARYL ALCOHOL; CETEARYL GLUCOSIDE; C13-14 ISOPARAFFIN; PHENOXYETHANOL; POLYACRYLAMIDE (1500 MW); LOBELIA INFLATA LEAF; MENTHOL; XANTHAN GUM; VACCINIUM ANGUSTIFOLIUM LEAF; GLYCERIN

ROOVEMAG Magnesium Soothing Warming Cream

Active ingredients
Arnica Montana (Arnica) 1X
Hamamelis Virginiana (Witch Hazel) 1X
Magnesia Sulphurica (Magnesium Sulfate) 1X

Purpose

Pain, inflammation

Pain, Fatigue

Pain

Uses

Natural temporary relief for aches, pains and inflammation from minor injuries, overexertion and fatigue.

Warnings

For external use only. Do not use on broken skin or open wounds.

Stop and ask a doctor if

Pain Persists for more than 5 days

- If pain, redness, or swelling worsens
- if new symptoms occur
  If pregnant or Breast-feeding, ask a health professional before use.

Keep out of reach of children. If swallowed, get medical help or contact a poison control center right away.

PREGNANCY OR BREAST FEEDING

If pregnant or Breast-feeding, ask a health professional before use.

Keep out of reach of children. If swallowed, get medical help or contact a poison control center right away.

Directions

Adults and children over the age of 2 years old: Apply generously with gentle rubbing to the affected area 2 - 3 times daily or as needed.

Children less than 2 years of age: Consult a doctor.

Inactive ingredients

Butyrospermum Parkii (Shea) Butter, C13-14 Isoparaffin, Capsicum Frutescens (Pepper) Fruit Extract, Cetearyl Alcohol, Cetearyl Glucoside, Deionized Water, Emulsifying Wax, Fragrance, Glycerin, Laureth-7, Lobelia Inflata Extract, Mangifera Indica (Mango) Seed Butter, Mentha piperita (Peppermint) Leaf Oil, Menthol, Olea Europaea (Olive) Fruit Oil, Phenoxyethanol, Polyacrylamide, Sodium Hyaluronate (Hyaluronic) Acid, Tripeptide Marine Collagen, Vaccinium Angustifolium (Blueberry) Fruit Extract, Vegetable Oil, Xanthan Gum.

Questions or Comments

Contact: contact@tijara.llc

Tijara, LLC

447 Broadway,

2nd Floor Suite #1188

New York, New York 10013,

United States

Uses

Natural temporary relief for aches, pains and inflammation from minor injuries, overexertion and fatigue.

Directions

Adults and children over the age of 2 years old: Apply generously with gentle rubbing to the affected area 2-3 times daily or as needed.

Children less than 2 years of age: Consult a doctor.

ROOVEMAG Magnesium Soothing Cream 60 ml LABEL

MULTI-LAYER LABEL FOR ROOVEMAG CREAM 60 ML